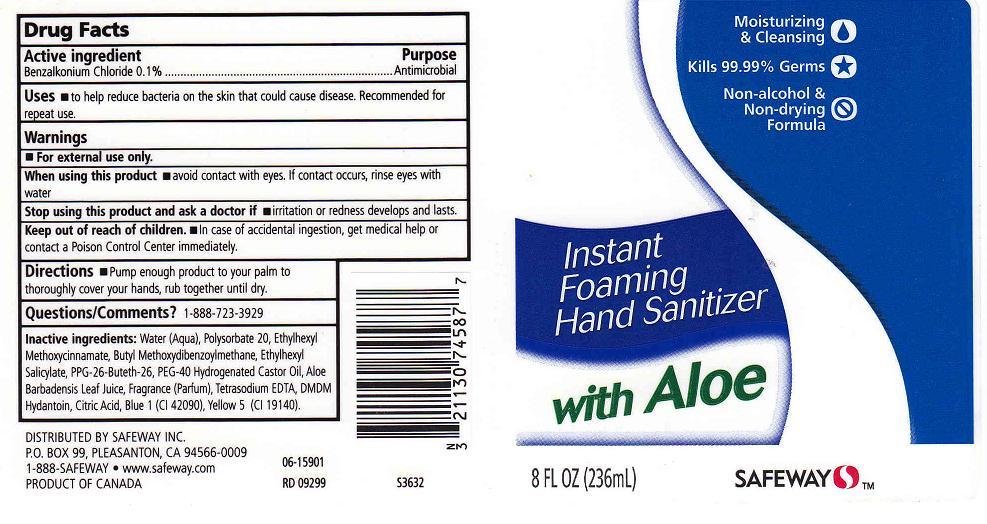 DRUG LABEL: FOAMING HAND SANITIZER
NDC: 21130-240 | Form: LIQUID
Manufacturer: SAFEWAY INC
Category: otc | Type: HUMAN OTC DRUG LABEL
Date: 20100714

ACTIVE INGREDIENTS: BENZALKONIUM CHLORIDE 0.1000 mL/100 mL

DRUG FACTS BOX (BACK LABEL)

ACTIVE INGREDIENT

BENZALKONIUM CHLORIDE 0.1% (ANTISEPTIC)

USES AND DIRECTIONS

- USES: TO HELP REDUCE BACTERIA ON THE SKIN THAT COULD CAUSE DISEASE. RECOMMENDED FOR REPEATED USE.
- DIRECTIONS: PUMP ENOUGH PRODUCT TO YOUR PALM TO THOROUGHLY COVER YOUR HANDS, RUB TOGETHER UNTIL DRY.

WARNINGS

- FOR EXTERNAL USE ONLY.

WHEN USING THIS PRODUCT

- AVOID CONTACT WITH EYES. IF CONTACT OCCURS, RINSE EYES WITH WATER.

STOP USE AND ASK A DOCTOR IF

- SKIN IRRITATION OR REDNESS DEVELOPS AND LASTS.

KEEP OUT OF REACH OF CHILDREN

- IN CASE OF ACCIDENTAL INGESTION, GET MEDICAL HELP OR CONTACT A POISON CONTROL CENTER IMMEDIATELY.

PACKAGE FRONT AND BACK LABELS

- 8OZ FRONT AND BACK LABELS: safeway8.jpg

QUESTIONS/COMMENTS?

1-888-723-3929